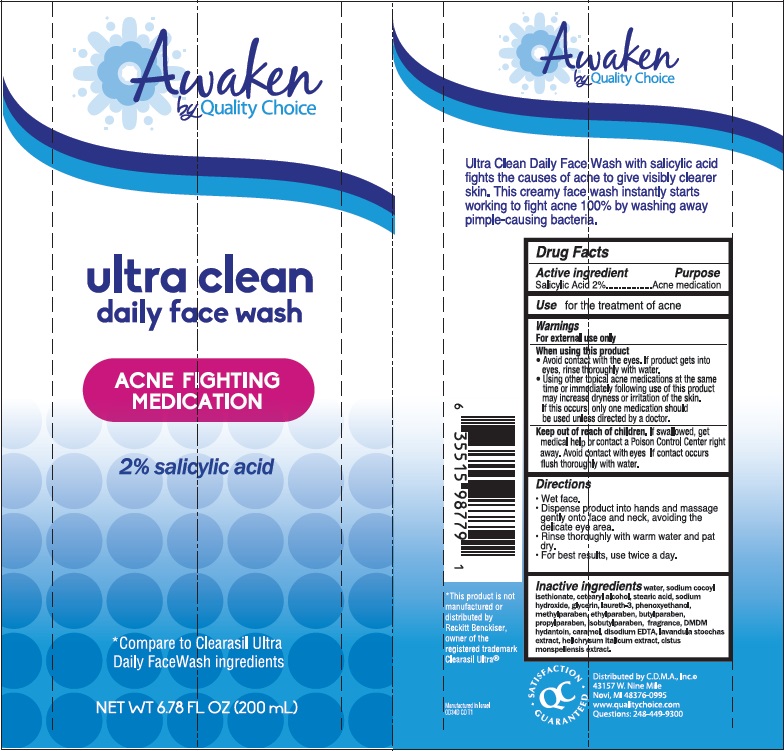 DRUG LABEL: Awaken by Quality Choice Ultra Clean Daily Face Wash
NDC: 63868-250 | Form: CREAM
Manufacturer: Chain Drug Marketing Association
Category: otc | Type: HUMAN OTC DRUG LABEL
Date: 20141001

ACTIVE INGREDIENTS: SALICYLIC ACID 2 g/100 g
INACTIVE INGREDIENTS: WATER; SODIUM COCOYL ISETHIONATE; CETOSTEARYL ALCOHOL; STEARIC ACID; SODIUM HYDROXIDE; GLYCERIN; LAURETH-3; PHENOXYETHANOL; METHYLPARABEN; ETHYLPARABEN; BUTYLPARABEN; PROPYLPARABEN; ISOBUTYLPARABEN; DMDM HYDANTOIN; CARAMEL; EDETATE DISODIUM; LAVANDULA STOECHAS FLOWERING TOP; HELICHRYSUM ITALICUM FLOWER; CISTUS MONSPELIENSIS LEAF

Awaken by Quality Choice ultra clean daily face wash

Active ingredient

Salicylic Acid 2%

Purpose

Acne medication

Indications

- for the treatment of acne

Warnings

For external use only.

When using this product

- Avoid contact with the eyes. If product gets into eyes, rinse thoroughly with water.
- Using other topical acne medications at the same time or immediately following use of this product may increase dryness or irritation of the skin. If this occurs, only one medication should be used unless directed by a doctor.

Keep Out of Reach of Children.

If swallowed, get medical help or contact a Poison Control Center right away. Avoid contact with eyes If contact occurs flush thoroughly with water.

Directions

- Wet face.
- Dispense product into hands and massage gently onto face and neck, avoiding the delicate eye area.
- Rinse thoroughly with warm water and pat dry.
- For best results, use twice a day.

Inactive ingredients

water, sodium cocoyl isethionate, cetearyl alcohol, stearic acid, sodium hydroxide, glycerin, laureth-3, phenoxyethanol, methylparaben, ethylparaben, butylparaben, propylparaben, isobutylparaben, fragrance, DMDM hydantoin, caramel, disodium EDTA, lavandula stoechas extract, helichrysum italicum extract, cistus monspeliensis extract.

Package/Label Principal Display Panel

Awaken
by Quality Choice

ultra clean
daily face wash

ACNE FIGHTING
MEDICATION

2% salicylic acid

*Compare to Clearasil Ultra
Daily FaceWash ingredients

NET WT 6.78 FL OZ (200 mL)

Ultra Clean Daily Face Wash with salicylic acid fights the causes of acne to give visibly clearer skin. This creamy face wash instantly starts working to fight acne 100% by washing away pimple-causing bacteria.

*This product is not manufactured or distributed by Reckitt Benckiser, owner of the registered trademark Clearasil Ultra®

Distributed by C.D.M.A., Inc.©
43157 W. Nine Mile
Novi, MI 48376-0995
www.qualitychoice.com
Questions: 248-449-9300

SATISFACTION GUARANTEED

Manufactured in Israel
0D34D CD T1

Carton Label